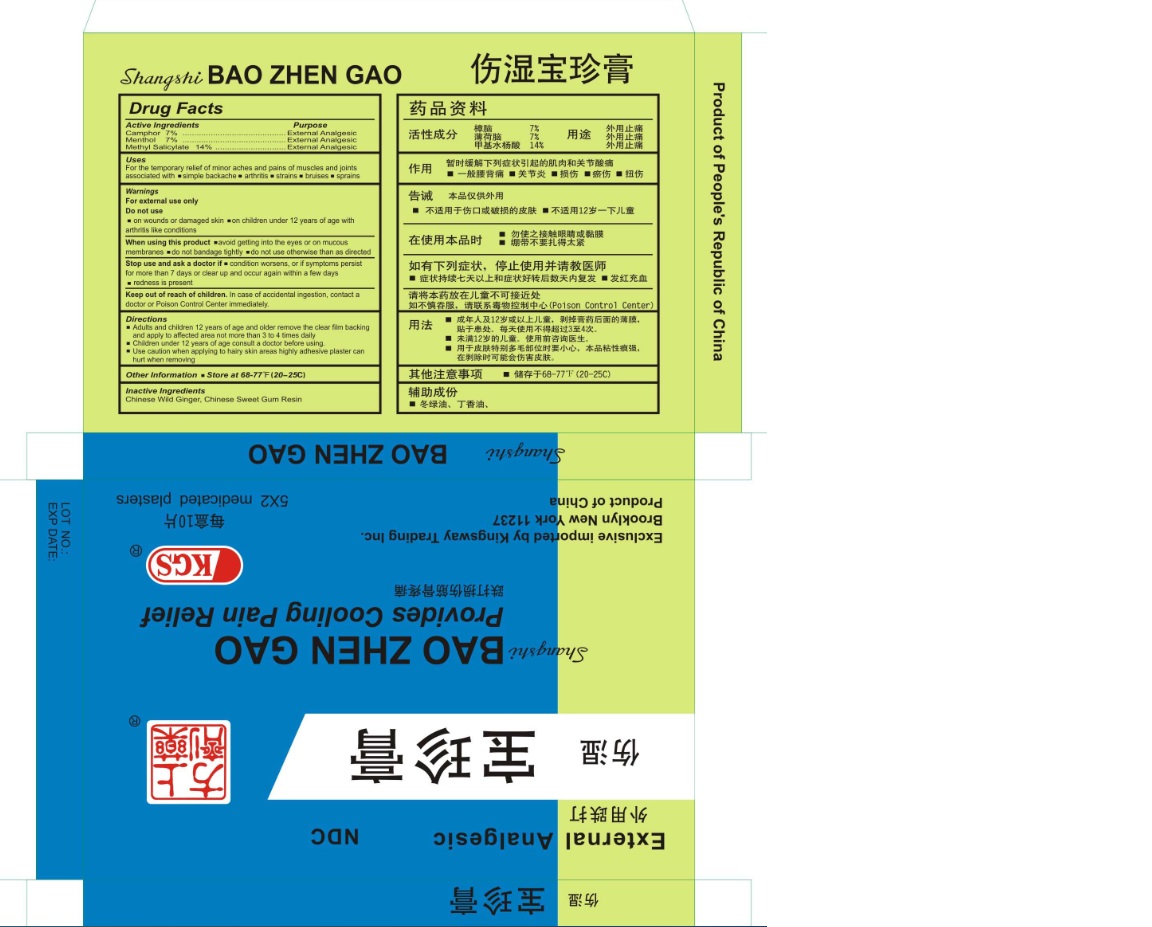 DRUG LABEL: KGS Bao Zhen Gao
NDC: 70551-002 | Form: PATCH
Manufacturer: Huangshi Likang Pharmaceutical Co.,Ltd.
Category: otc | Type: HUMAN OTC DRUG LABEL
Date: 20160527

ACTIVE INGREDIENTS: METHYL SALICYLATE 14 g/1 1; MENTHOL 7 g/1 1; CAMPHOR (SYNTHETIC) 7 g/1 1
INACTIVE INGREDIENTS: LIQUIDAMBAR STYRACIFLUA RESIN; ASARUM SIEBOLDII

Drug Facts

Active Ingredients

Camphor 11%

Menthol 9%

Methyl Salicylate 13%

Purpose

External Analgesic

External Analgesic

External Analgesic

Uses

For the temporarily relief of minor pains and aches of muscles and joints associated with ■ simple backache ■ arthritis ■ strains

■ bruises ■ sprains

Warnings

For external use only

Do not use

■ on wounds or damaged skin ■on children under 12 years of age with arthritis like conditions

When using this product

■ avoid contact with the eyes or on mucus membranes ■ do not bandage tightly ■ do not use otherwise than as directed

Stop use and ask a doctor if

■ condition worsens or symptoms persist for more than 7 days or clear up and occur again within a few days ■ redness is present

Keep out of reach of children

in case of accidental ingestion, contact a Poison Control Center immediately

Directions

■ Adults and children 12 years of age and older remove the clear film backing and apply to affected area not more than 3 to 4 times daily

■ Children under 12 years of age consult a doctor before using

■ Use caution when applying to hairy skin areas, highly adhesive plaster can hurt when removing

Other Information

■ Store at 68-77F (20-25C)

Inactive Ingredients

Chinese Wild Ginger, Chinese Sweet Gum Resin